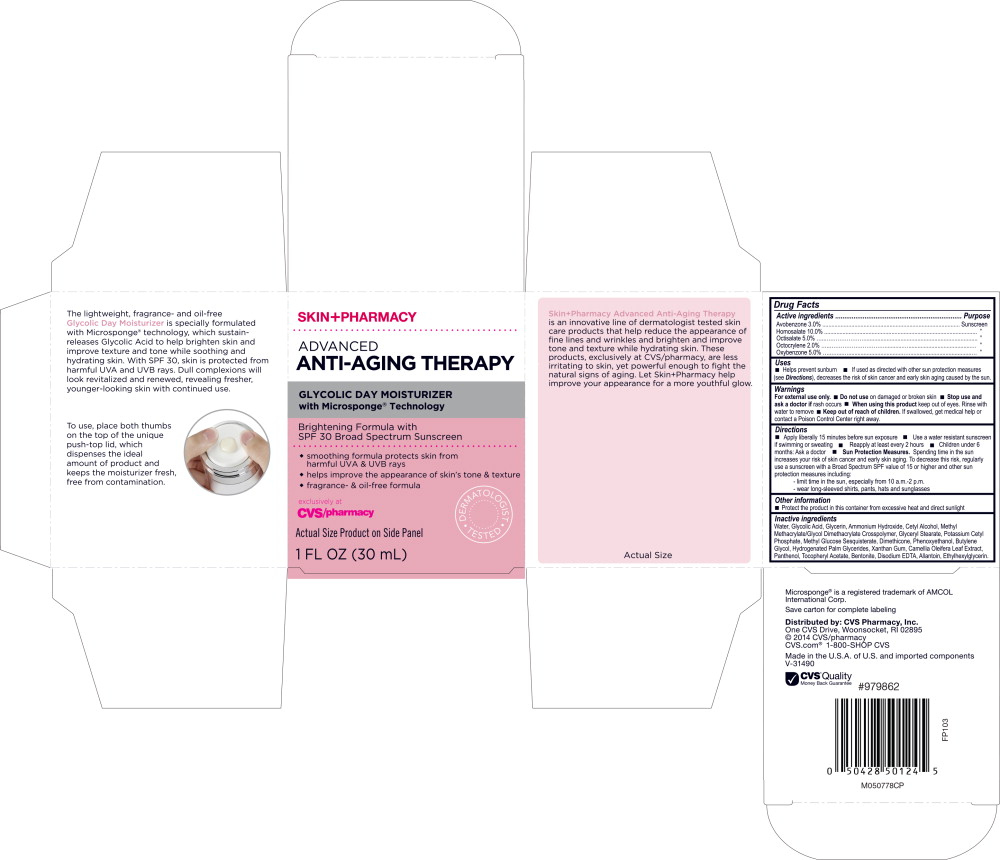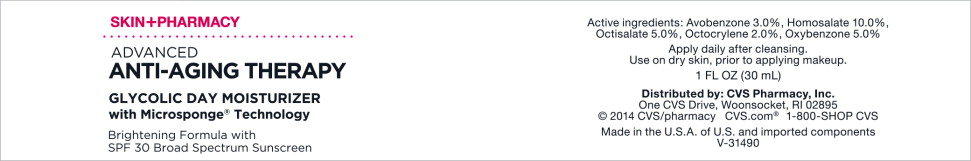 DRUG LABEL: SkinPharmacy Advanced Anti-Aging Therapy Glycolic Day Moisturizer SPF 30
NDC: 69842-079 | Form: LOTION
Manufacturer: CVS Health
Category: otc | Type: HUMAN OTC DRUG LABEL
Date: 20170308

ACTIVE INGREDIENTS: homosalate 100 mg/1 mL; octisalate 50 mg/1 mL; avobenzone 30 mg/1 mL; octocrylene 20 mg/1 mL; oxybenzone 50 mg/1 mL
INACTIVE INGREDIENTS: water; glycolic acid; glycerin; Ammonia; cetyl alcohol; methyl methacrylate/glycol dimethacrylate crosspolymer; glyceryl monostearate; potassium cetyl phosphate; dimethicone; Hydrogenated Palm glycerides; allantoin; butylene glycol; Ethylhexylglycerin; phenoxyethanol; Panthenol; .ALPHA.-TOCOPHEROL ACETATE, DL-; Bentonite; Xanthan gum; Camellia Oleifera Leaf; Edetate disodium

Drug Facts

Active ingredients

Avobenzone 3.0%

Homosalate 10.0%

Octisalate 5.0%

Octocrylene 2.0%

Oxybenzone 5.0%

Purpose

Sunscreen

”

”

”

”

Uses

- Helps prevent sunburn
- If used as directed with other sun protection measures (see Directions), decreases the risk of skin cancer and early skin aging cause by the sun.

Warnings

For external use only.

- Do not use on damaged or broken skin

- Stop use and ask a doctor if rash occurs

- When using this product keep out of eyes. Rinse with water to remove.

- Keep out of reach of children. If swallowed, get medical help or contact a Poison Control Center right away.

Directions

- Apply liberally 15 minutes before sun exposure
- Use a water resistant sunscreen if swimming or sweating
- Reapply at least every 2 hours
- Children under 6 months: Ask a doctor
- Sun Protection Measures. Spending time in the sun increases your risk of skin cancer and early skin aging. To decrease this risk, regularly use a sunscreen with a Broad Spectrum SPF value of 15 or higher and other sun protection measures including:
  - limit time in the sun, especially from 10 a.m.-2 p.m.
  - wear long-sleeved shirts, pants, hats and sunglasses

Other information

- Protect the product in this container from excessive heat and direct sunlight

Inactive ingredients

Water, Glycolic Acid, Glycerin, Ammonium Hydroxide, Cetyl Alcohol, Methyl Methacrylate/Glycol Dimethacrylate Crosspolymer, Glyceryl Stearate, Potassium Cetyl Phosphate, Methyl Glucose Sesquistearate, Dimethicone, Phenoxyethanol, Butylene Glycol, Hydrogenated Palm Glycerides, Xanthan Gum, Camellia Oleifera Leaf Extract, Panthenol, Tocopheryl Acetate, Bentonite, Disodium EDTA, Allantoin, Ethylhexylglycerin.

Microsponge® is a registered trademark of AMCOL International Corp.

Save carton for complete labeling.

Distributed by: CVS Pharmacy, Inc.

One CVS Drive, Woonsocket, RI 02895

© 2014 CVS/pharmacy

CVS.com® 1-800-SHOP CVS

Made in the U.S.A. of U.S. and imported components V-31490

CVS® Quality

Money Back Guarantee

#979862

M050778CP

FP103

Principal Display Panel - Carton Label

SKIN+PHARMACY

ADVANCED
ANTI-AGING THERAPY

GLYCOLIC DAY MOISTURIZER
with Microsponge® Technology

Brightening Formula with
SPF 30 Broad Spectrum Screen

- smoothing formula protects skin from harmful UVA & UVB rays
- helps improve the appearance of skin's tone & texture
- fragrance- & oil-free formula

exclusively at
CVS/pharmacy

DERMATOLOGIST TESTED

Actual Size Product on Side Panel

1 FL OZ (30 mL)

Principal Display Panel - Jar Label

SKIN+PHARMACY

ADVANCED
ANTI-AGING THERAPY

GLYCOLIC DAY MOISTURIZER
with Microsponge® Technology

Brightening Formula with
SPF 30 Broad Spectrum Sunscreen